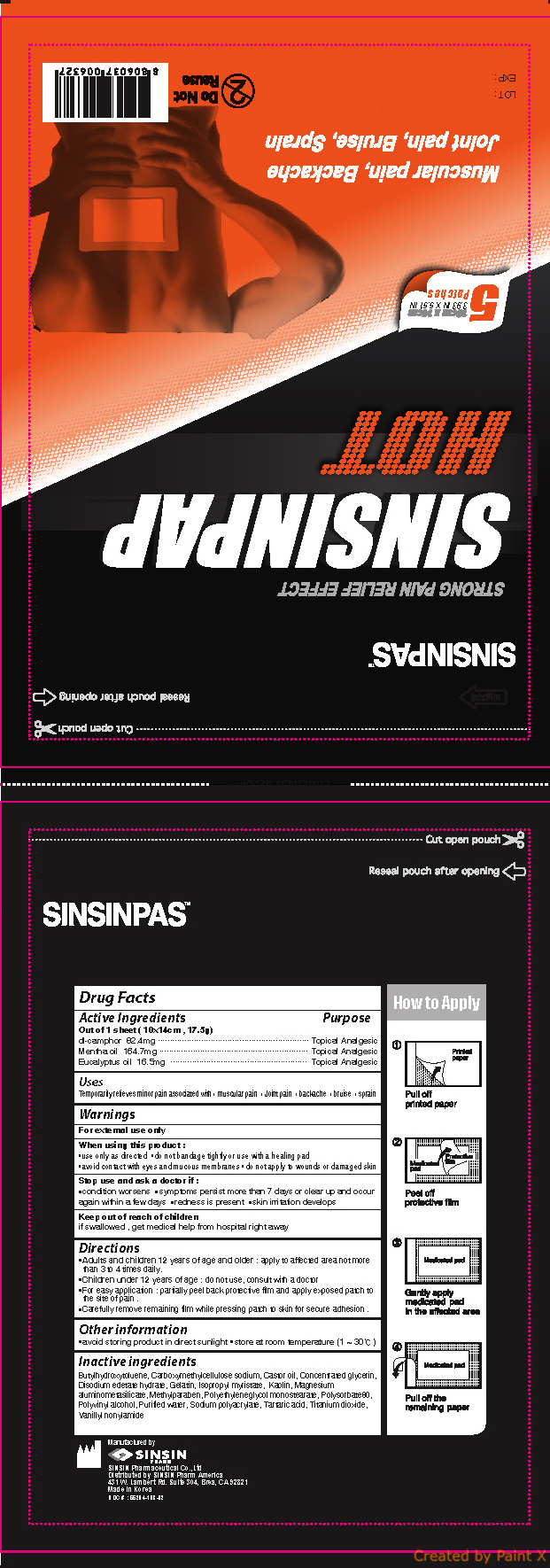 DRUG LABEL: SINSINPAP HOT
NDC: 55264-103 | Form: PATCH
Manufacturer: Sinsin Pharmaceutical Co., Ltd.
Category: otc | Type: HUMAN OTC DRUG LABEL
Date: 20240105

ACTIVE INGREDIENTS: EUCALYPTUS OIL 16.5 mg/17.5 g; CAMPHOR (SYNTHETIC) 82.4 mg/17.5 g; PEPPERMINT OIL 164.7 mg/17.5 g
INACTIVE INGREDIENTS: WATER; SODIUM POLYACRYLATE (8000 MW); NONIVAMIDE; BUTYLATED HYDROXYTOLUENE; ISOPROPYL MYRISTATE; KAOLIN; SILODRATE; METHYLPARABEN; POLYVINYL ALCOHOL, UNSPECIFIED; CARBOXYMETHYLCELLULOSE SODIUM, UNSPECIFIED FORM; CASTOR OIL; GELATIN; POLYSORBATE 80; TARTARIC ACID; TITANIUM DIOXIDE

SINSINPAP HOT

Active ingredients

Dl- camphor 82.4mg

Mentha oil 164.7mg

Eucalyptus oil 16.5mg

Purpose

Topical Analgesic

Uses

Temporarily relieves minor pain associated with • muscular pain • Joint pain • backache • bruise • sprain

Warnings

For external use only

When using this product :

• use only as directed • do not bandage tightly or use with a healing pad
• avoid contact with eyes and mucous membranes • do not apply to wounds or damaged skin

Stop use and ask a doctor if :

• condition worsens • symptoms persist more than 7 days or clear up and occur again within a few days • redness is present • skin irritation develops

Keep out of reach of children

if swallowed , get medical help from hospital right away

Directions

• Adults and children 12 years of age and older : apply to affected area not more than 3 to 4 times daily.
• Children under 12 years of age : do not use, consult with a doctor
• For easy application : partially peel back protective film and apply exposed patch to the site of pain .
• Carefully remove remaining film while pressing patch to skin for secure adhesion .

Inactive ingredients

Butylhydroxytoluene, Carboxymethylcellulose sodium, Castor oil, Concentrated glycerin, Disodium edetate hydrate, Gelatin, Isopropyl myristate, Kaolin, Magnesium aluminometasilicate, Methylparaben, Polyethyleneglycol monostearate, Polysorbate80, Polyvinyl alcohol, Purified water, Sodium polyacrylate, Tartaric acid, Titanium dioxide, Vanillyl nonylamide